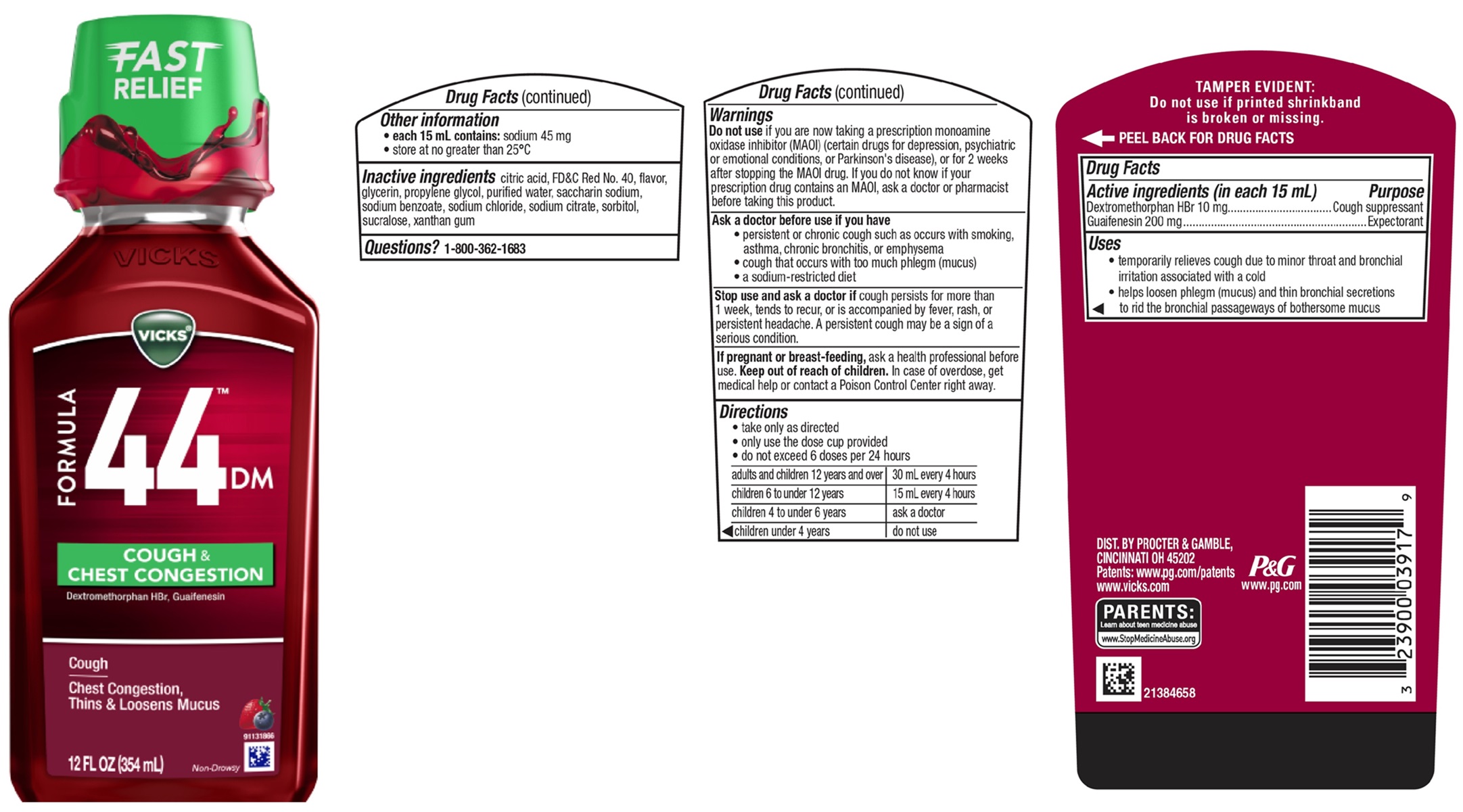 DRUG LABEL: VICKS FORMULA 44DM
NDC: 69423-810 | Form: LIQUID
Manufacturer: The Procter & Gamble Manufacturing Company
Category: otc | Type: HUMAN OTC DRUG LABEL
Date: 20251202

ACTIVE INGREDIENTS: DEXTROMETHORPHAN HYDROBROMIDE 10 mg/15 mL; GUAIFENESIN 200 mg/15 mL
INACTIVE INGREDIENTS: SODIUM BENZOATE; SUCRALOSE; XANTHAN GUM; SODIUM CHLORIDE; SORBITOL; CITRIC ACID MONOHYDRATE; FD&C RED NO. 40; PROPYLENE GLYCOL; WATER; GLYCERIN; SACCHARIN SODIUM; SODIUM CITRATE

VICKS® FORMULA 44™DM
COUGH & CHEST CONGESTION

Drug Facts

Active ingredient (in each 15 mL)

Dextromethorphan HBr 10 mg

Guaifenesin 200 mg

Purpose

Cough suppressant

Expectorant

Uses

- temporarily relieves cough due to minor throat and bronchial irritation associated with a cold
- helps loosen phlegm (mucus) and thin bronchial secretions to rid the bronchial passageways of bothersome mucus

Warnings

DO NOT USE

Do not useif you are now taking a prescription monoamine oxidase inhibitor (MAOI) (certain drugs for depression, psychiatric or emotional conditions, or Parkinson's disease), or for 2 weeks after stopping the MAOI drug. If you do not know if your prescription drug contains an MAOI, ask a doctor or pharmacist before taking this product.

Ask a doctor before use if you have

- persistent or chronic cough such as occurs with smoking, asthma, chronic bronchitis, or emphysema
- cough that occurs with too much phlegm (mucus)
- a sodium-restricted diet

Stop use and ask a doctor if

cough persists for more than 1 week, tends to recur, or is accompanied by fever, rash, or persistent headache. A persistent cough may be a sign of a serious condition.

If pregnant or breast-feeding,

ask a health professional before use.

Keep out of reach of children.

OVERDOSAGE

In case of overdose, get medical help or contact a Poison Control Center right away.

Directions

• take only as directed
• only use the dose cup provided
• do not exceed 6 doses per 24 hours

adults and children 12 years and over | 30 mL every 4 hours
children 6 to under 12 years | 15 mL every 4 hours
children 4 to under 6 years | ask a doctor
children under 4 years | do not use

Other information

• each 15 mL contains:sodium 45 mg
• store at no greater than 25°C

Inactive ingredients

citric acid, FD&C Red No. 40, flavor, glycerin, propylene glycol, purified water, saccharin sodium, sodium benzoate, sodium chloride, sodium citrate, sorbitol, sucralose, xanthan gum

Questions?

1-800-362-1683

TAMPER EVIDENT: Do not use if printed shrinkband is broken or missing.

DIST. BY PROCTER & GAMBLE,
CINCINNATI OH 45202

PRINCIPAL DISPLAY PANEL - 354 ml Bottle Label

VICKS ®

FORMULA 44™ DM

COUGH &

CHEST CONGESTION

Dextromethorphan HBr, Guaifenesin

Cough

Chest Congestion, Thins & Loosens Mucus

Non-Drowsy

12 FL OZ (354 ml)